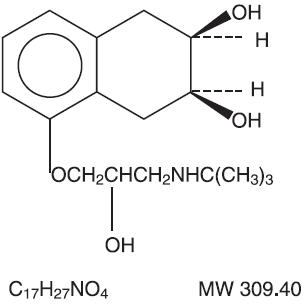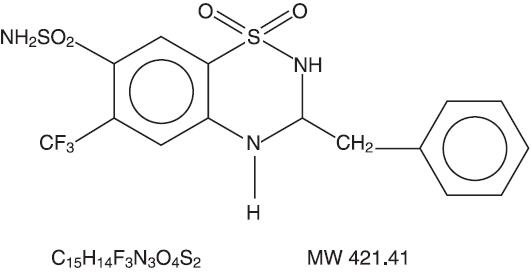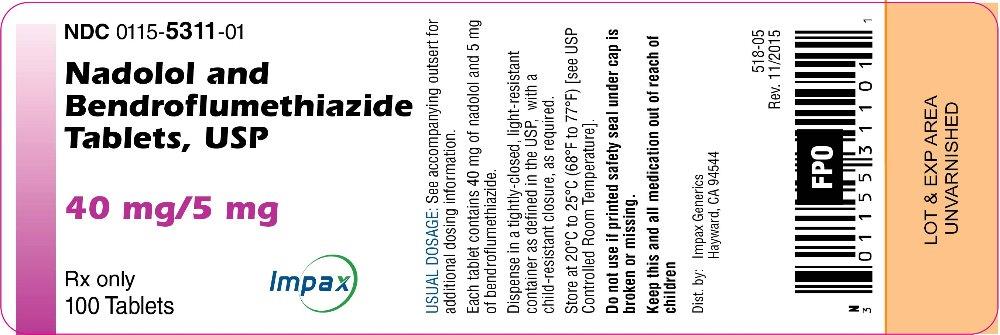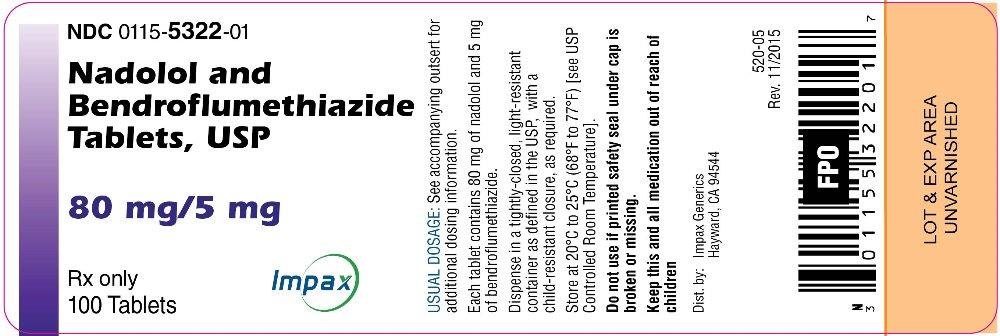 DRUG LABEL: Nadolol and Bendroflumethiazide
NDC: 0115-5311 | Form: TABLET
Manufacturer: Impax Generics
Category: prescription | Type: HUMAN PRESCRIPTION DRUG LABEL
Date: 20160415

ACTIVE INGREDIENTS: NADOLOL 40 mg/1 1; BENDROFLUMETHIAZIDE 5 mg/1 1
INACTIVE INGREDIENTS: CROSCARMELLOSE SODIUM; HYPROMELLOSES; LACTOSE MONOHYDRATE; MAGNESIUM STEARATE; MANNITOL; CELLULOSE, MICROCRYSTALLINE; STARCH, CORN; TALC

NADOLOL AND
BENDROFLUMETHIAZIDE
TABLETS, USP,
40 mg/5 mg AND 80 mg/5 mg

Rx only

DESCRIPTION

Nadolol and bendroflumethiazide tablets for oral administration combine two antihypertensive agents: nadolol, a nonselective beta-adrenergic blocking agent, and bendroflumethiazide, a thiazide diuretic-antihypertensive.

Each tablet contains 40 mg or 80 mg nadolol combined with 5 mg bendroflumethiazide. Inactive ingredients: croscarmellose sodium, hypromellose (type 2910), lactose monohydrate, magnesium stearate, mannitol, microcrystalline cellulose, pregelatinized starch and talc.

Nadolol

Nadolol is a white crystalline powder. It is freely soluble in ethanol, soluble in hydrochloric acid, slightly soluble in water and in chloroform, and very slightly soluble in sodium hydroxide.

Nadolol is designated chemically as 1-(tert-butylamino)-3-{(5,6,7,8-tetrahydro-cis-6,7-dihydroxy-1-naphthyl)oxy}-2-propanol. Structural formula:

Bendroflumethiazide

Bendroflumethiazide is a white crystalline powder. It is soluble in alcohol and in sodium hydroxide, and insoluble in hydrochloric acid, water, and chloroform.

Bendroflumethiazide is designated chemically as 3-benzyl-3,4-dihydro-6-(trifluoromethyl)-2H-1,2,4-benzothiadiazine-7-sulfonamide 1,1-dioxide. Structural formula:

CLINICAL PHARMACOLOGY

Nadolol

Nadolol is a nonselective beta-adrenergic receptor blocking agent. Clinical pharmacology studies have demonstrated beta-blocking activity by showing (1) reduction in heart rate and cardiac output at rest and on exercise, (2) reduction of systolic and diastolic blood pressure at rest and on exercise, (3) inhibition of isoproterenol-induced tachycardia, and (4) reduction of reflex orthostatic tachycardia.

Nadolol specifically competes with beta-adrenergic receptor agonists for available beta receptor sites; it inhibits both the beta1 receptors located chiefly in cardiac muscle and the beta2 receptors located chiefly in the bronchial and vascular musculature, inhibiting the chronotropic, inotropic, and vasodilator responses to beta-adrenergic stimulation proportionately. Nadolol has no intrinsic sympathomimetic activity and, unlike some other beta-adrenergic blocking agents, nadolol has little direct myocardial depressant activity and does not have an anesthetic-like membrane-stabilizing action. Animal and human studies show that nadolol slows the sinus rate and depresses AV conduction. In dogs, only minimal amounts of nadolol were detected in the brain relative to amounts in blood and other organs and tissues. Nadolol has low lipophilicity as determined by octanol/water partition coefficient, a characteristic of certain beta-blocking agents that has been correlated with the limited extent to which these agents cross the blood-brain barrier, their low concentration in the brain, and low incidence of CNS-related side effects.

In controlled clinical studies, nadolol at doses of 40 to 320 mg/day has been shown to decrease both standing and supine blood pressure, the effect persisting for approximately 24 hours after dosing.

The mechanism of the antihypertensive effects of beta-adrenergic receptor blocking agents has not been established; however, factors that may be involved include (1) competitive antagonism of catecholamines at peripheral (non-CNS) adrenergic neuron sites (especially cardiac) leading to decreased cardiac output, (2) a central effect leading to reduced tonic-sympathetic nerve outflow to the periphery, and (3) suppression of renin secretion by blockade of the beta-adrenergic receptors responsible for renin release from the kidneys.

While cardiac output and arterial pressure are reduced by nadolol therapy, renal hemodynamics are stable, with preservation of renal blood flow and glomerular filtration rate.

By blocking catecholamine-induced increases in heart rate, velocity and extent of myocardial contraction, and blood pressure, nadolol generally reduces the oxygen requirements of the heart at any given level of effort, making it useful for many patients in the long-term management of angina pectoris. On the other hand, nadolol can increase oxygen requirements by increasing left ventricular fiber length and end diastolic pressure, particularly in patients with heart failure.

Although beta-adrenergic receptor blockade is useful in treatment of angina and hypertension, there are also situations in which sympathetic stimulation is vital. For example, in patients with severely damaged hearts, adequate ventricular function may depend on sympathetic drive. Beta2-adrenergic blockade may worsen AV block by preventing the necessary facilitating effects of sympathetic activity on conduction. Beta2-adrenergic blockade results in passive bronchial constriction by interfering with endogenous adrenergic bronchodilator activity in patients subject to bronchospasm and may also interfere with exogenous bronchodilators in such patients.

Absorption of nadolol after oral dosing is variable, averaging about 30 percent. Peak serum concentrations of nadolol usually occur in three to four hours after oral administration and the presence of food in the gastrointestinal tract does not affect the rate or extent of nadolol absorption. Approximately 30 percent of the nadolol present in serum is reversibly bound to plasma protein.

Unlike many other beta-adrenergic blocking agents, nadolol is not metabolized by the liver and is excreted unchanged, principally by the kidneys.

The half-life of therapeutic doses of nadolol is about 20 to 24 hours, permitting once-daily dosage. Because nadolol is excreted predominantly in the urine, its half-life increases in renal failure (see PRECAUTIONS, General, and DOSAGE AND ADMINISTRATION). Steady state serum concentrations of nadolol are attained in six to nine days with once-daily dosage in persons with normal renal function. Because of variable absorption and different individual responsiveness, the proper dosage must be determined by titration.

Exacerbation of angina and, in some cases, myocardial infarction and ventricular dysrhythmias have been reported after abrupt discontinuation of therapy with beta-adrenergic blocking agents in patients with coronary artery disease. Abrupt withdrawal of these agents in patients without coronary artery disease has resulted in transient symptoms, including tremulousness, sweating, palpitation, headache, and malaise. Several mechanisms have been proposed to explain these phenomena, among them increased sensitivity to catecholamines because of increased numbers of beta receptors.

Bendroflumethiazide

The mechanism of action of bendroflumethiazide results in an interference with the renal tubular mechanism of electrolyte reabsorption. At maximal therapeutic dosage all thiazides are approximately equal in their diuretic potency.

Thiazides increase excretion of sodium and chloride in approximately equivalent amounts. Natriuresis causes a secondary loss of potassium and bicarbonate.

The mechanism of the antihypertensive effect of thiazides is unknown. Thiazides do not affect normal blood pressure.

Onset of action of thiazides occurs in two hours and the peak effect at about four hours. Duration of action persists for approximately six to 12 hours. Thiazides are eliminated rapidly by the kidney.

INDICATIONS

Nadolol and bendroflumethiazide tablets are indicated for the treatment of hypertension, to lower blood pressure. Lowering blood pressure reduces the risk of fatal and nonfatal cardiovascular events, primarily strokes and myocardial infarctions. These benefits have been seen in controlled trials of antihypertensive drugs from a wide variety of pharmacologic classes including the classes to which this drug principally belongs. There are no controlled trials demonstrating risk reduction with nadolol and bendroflumethiazide tablets.

Control of high blood pressure should be part of comprehensive cardiovascular risk management, including, as appropriate, lipid control, diabetes management, antithrombotic therapy, smoking cessation, exercise, and limited sodium intake. Many patients will require more than one drug to achieve blood pressure goals. For specific advice on goals and management, see published guidelines, such as those of the National High Blood Pressure Education Program's Joint National Committee on Prevention, Detection, Evaluation, and Treatment of High Blood Pressure (JNC).

Numerous antihypertensive drugs, from a variety of pharmacologic classes and with different mechanisms of action, have been shown in randomized controlled trials to reduce cardiovascular morbidity and mortality, and it can be concluded that it is blood pressure reduction, and not some other pharmacologic property of the drugs, that is largely responsible for those benefits. The largest and most consistent cardiovascular outcome benefit has been a reduction in the risk of stroke, but reductions in myocardial infarction and cardiovascular mortality also have been seen regularly.

Elevated systolic or diastolic pressure causes increased cardiovascular risk, and the absolute risk increase per mmHg is greater at higher blood pressures, so that even modest reductions of severe hypertension can provide substantial benefit. Relative risk reduction from blood pressure reduction is similar across populations with varying absolute risk, so the absolute benefit is greater in patients who are at higher risk independent of their hypertension (for example, patients with diabetes or hyperlipidemia), and such patients would be expected to benefit from more aggressive treatment to a lower blood pressure goal.

Some antihypertensive drugs have smaller blood pressure effects (as monotherapy) in black patients, and many antihypertensive drugs have additional approved indications and effects (e.g., on angina, heart failure, or diabetic kidney disease). These considerations may guide selection of therapy.

Nadolol and bendroflumethiazide tablets are not indicated for initial therapy of hypertension. If the fixed combination represents the dose titrated to the individual patient's needs, it may be more convenient than the separate components.

CONTRAINDICATIONS

Nadolol

Nadolol is contraindicated in bronchial asthma, sinus bradycardia and greater than first degree conduction block, cardiogenic shock, and overt cardiac failure (see WARNINGS).

Bendroflumethiazide

Bendroflumethiazide is contraindicated in anuria. It is also contraindicated in patients who have previously demonstrated hypersensitivity to bendroflumethiazide or other sulfonamide-derived drugs.

WARNINGS

Nadolol

Cardiac Failure

Sympathetic stimulation may be a vital component supporting circulatory function in patients with congestive heart failure, and its inhibition by beta-blockade may precipitate more severe failure. Although beta-blockers should be avoided in overt congestive heart failure, if necessary, they can be used with caution in patients with a history of failure who are well compensated, usually with digitalis and diuretics. Beta-adrenergic blocking agents do not abolish the inotropic action of digitalis on heart muscle.

IN PATIENTS WITHOUT A HISTORY OF HEART FAILURE, continued use of beta-blockers can, in some cases, lead to cardiac failure. Therefore, at the first sign or symptom of heart failure, the patient should be digitalized and/ or treated with diuretics, and the response observed closely, or nadolol should be discontinued (gradually, if possible).

Exacerbation of Ischemic Heart Disease Following Abrupt Withdrawal

Hypersensitivity to catecholamines has been observed in patients withdrawn from beta-blocker therapy; exacerbation of angina and, in some cases, myocardial infarction have occurred after abrupt discontinuation of such therapy. When discontinuing chronically administered nadolol, particularly in patients with ischemic heart disease, the dosage should be gradually reduced over a period of one to two weeks and the patient should be carefully monitored. If angina markedly worsens or acute coronary insufficiency develops, nadolol administration should be reinstituted promptly, at least temporarily, and other measures appropriate for the management of unstable angina should be taken. Patients should be warned against interruption or discontinuation of therapy without the physician's advice. Because coronary artery disease is common and may be unrecognized, it may be prudent not to discontinue nadolol therapy abruptly even in patients treated only for hypertension.

Nonallergic Bronchospasm (e.g., chronic bronchitis, emphysema)

PATIENTS WITH BRONCHOSPASTIC DISEASES SHOULD IN GENERAL NOT RECEIVE BETA-BLOCKERS. Nadolol should be administered with caution since it may block bronchodilation produced by endogenous or exogenous catecholamine stimulation of beta2 receptors.

Major Surgery

Chronically administered beta-blocking therapy should not be routinely withdrawn prior to major surgery; however, the impaired ability of the heart to respond to reflex adrenergic stimuli may augment the risks of general anesthesia and surgical procedures.

Diabetes and Hypoglycemia

Beta-adrenergic blockade may prevent the appearance of premonitory signs and symptoms (e.g., tachycardia and blood pressure changes) of acute hypoglycemia. This is especially important with labile diabetics. Beta-blockade also reduces the release of insulin in response to hyperglycemia; therefore, it may be necessary to adjust the dose of antidiabetic drugs.

Thyrotoxicosis

Beta-adrenergic blockade may mask certain clinical signs (e.g., tachycardia) of hyperthyroidism. Patients suspected of developing thyrotoxicosis should be managed carefully to avoid abrupt withdrawal of beta-adrenergic blockade which might precipitate a thyroid storm.

Bendroflumethiazide

Thiazides should be used with caution in severe renal disease. In patients with renal disease, thiazides may precipitate azotemia. Cumulative effects of the drug may develop in patients with impaired renal function.

Thiazides should be used with caution in patients with impaired hepatic function or progressive liver disease, since minor alterations of fluid and electrolyte balance may precipitate hepatic coma.

Sensitivity reactions may occur in patients with or without a history of allergy or bronchial asthma.

The possibility of exacerbation or activation of systemic lupus erythematosus has been reported.

Lithium generally should not be given with diuretics; diuretic agents reduce the renal clearance of lithium and add a high risk of lithium toxicity. Refer to the package insert for lithium preparations before use of such concomitant therapy.

PRECAUTIONS

General

Nadolol

Nadolol should be used with caution in patients with impaired renal function (see DOSAGE AND ADMINISTRATION).

Bendroflumethiazide

Periodic determination of serum electrolytes to detect possible electrolyte imbalance should be performed at appropriate intervals.

All patients receiving thiazide therapy should be observed for clinical signs of fluid or electrolyte imbalance, namely: hyponatremia, hypochloremic alkalosis, and hypokalemia. Serum and urine electrolyte determinations are particularly important when the patient is vomiting excessively or receiving parenteral fluids. Warning signs or symptoms of fluid and electrolyte imbalance may include: dryness of the mouth, thirst, weakness, lethargy, drowsiness, restlessness, muscle pains or cramps, muscular fatigue, hypotension, oliguria, tachycardia, and gastrointestinal disturbances, such as nausea and vomiting.

Hypokalemia may develop, especially with brisk diuresis or when severe cirrhosis is present.

Interference with adequate oral electrolyte intake will also contribute to hypokalemia. Hypokalemia can sensitize or exaggerate the response of the heart to the toxic effects of digitalis (e.g., increased ventricular irritability). Concurrent administration of a potassium-sparing diuretic or potassium supplements may be indicated in these patients.

Any chloride deficit is generally mild and usually does not require specific treatment except under extraordinary circumstances (as in liver disease or renal disease). Dilutional hyponatremia may occur in edematous patients in hot weather; appropriate therapy is water restriction, rather than administration of salt, except in rare instances when the hyponatremia is life-threatening. In actual salt depletion, appropriate replacement is the therapy of choice.

Hyperuricemia may occur or frank gout may be precipitated in certain patients receiving thiazide therapy.

Latent diabetes mellitus may become manifest during thiazide administration.

The antihypertensive effect of thiazide diuretics may be enhanced in the postsympathectomy patient.

If progressive renal impairment becomes evident, as indicated by a rising nonprotein nitrogen or blood urea nitrogen (BUN), a careful reappraisal of therapy is necessary with consideration given to withholding or discontinuing diuretic therapy.

Thiazides may decrease serum PBI levels without signs of thyroid disturbance.

Calcium excretion is decreased by thiazides. Pathological changes in the parathyroid gland with hypercalcemia and hypophosphatemia have been observed in a few patients on prolonged thiazide therapy. The common complications of hyperparathyroidism such as renal lithiasis, bone resorption, and peptic ulceration have not been seen. Thiazides should be discontinued before carrying out tests for parathyroid function.

Thiazides have been shown to increase the urinary excretion of magnesium; this may result in hypomagnesemia.

Information for Patients

Patients, especially those with evidence of coronary artery insufficiency, should be warned against interruption or discontinuation of therapy without the physician's advice. Although cardiac failure rarely occurs in properly selected patients, patients being treated with beta-adrenergic blocking agents should be advised to consult the physician at the first sign or symptom of impending failure.

The patient should also be advised of a proper course in the event of an inadvertently missed dose.

The patient should be informed of symptoms that would suggest potential adverse effects and told to report them promptly.

Laboratory Tests

Serum electrolyte levels should be regularly monitored (see WARNINGS, Bendroflumethiazide, also PRECAUTIONS, General, Bendroflumethiazide).

Drug Interactions

Nadolol

When administered concurrently the following drugs may interact with beta-adrenergic receptor blocking agents:

Anesthetics, general-exaggeration of the hypotension induced by general anesthetics (see WARNINGS, Nadolol, Major Surgery).

Antidiabetic drugs (oral agents and insulin)-hypoglycemia or hyperglycemia; adjust dosage of antidiabetic drug accordingly (see WARNINGS, Nadolol, Diabetes and Hypoglycemia).

Catecholamine-depleting drugs (e.g., reserpine)- additive effect; monitor closely for evidence of hypotension and/or excessive bradycardia (e.g., vertigo, syncope, postural hypotension).

Response to Treatment for Anaphylactic Reaction-While taking beta-blockers, patients with a history of severe anaphylactic reaction to a variety of allergens may be more reactive to repeated challenge, either accidental, diagnostic, or therapeutic. Such patients may be unresponsive to the usual doses of epinephrine used to treat allergic reaction.

Bendroflumethiazide

When administered concurrently the following drugs may interact with thiazide diuretics:

Alcohol, barbiturates, or narcotics-potentiation of orthostatic hypotension may occur.

Amphotericin B, corticosteroids, or corticotropin (ACTH)-may intensify electrolyte imbalance, particularly hypokalemia. Monitor potassium levels; use potassium replacements if necessary.

Anticoagulants (oral)-dosage adjustments of anticoagulant medication may be necessary since bendroflumethiazide may decrease their effects.

Antigout medications-dosage adjustments of antigout medication may be necessary since bendroflumethiazide may raise the level of blood uric acid.

Other antihypertensive medications (e.g., ganglionic or peripheral adrenergic blocking agents)-dosage adjustments may be necessary since bendroflumethiazide may potentiate their effects.

Antidiabetic drugs (oral agents and insulin)-since thiazides may elevate blood glucose levels, dosage adjustments of antidiabetic agents may be necessary.

Calcium salts-increased serum calcium levels due to decreased excretion may occur. If calcium must be prescribed monitor serum calcium levels and adjust calcium dosage accordingly.

Cardiac glycosides-enhanced possibility of digitalis toxicity associated with hypokalemia. Monitor potassium levels; use potassium replacement if necessary.

Cholestyramine resin and colestipol HCl-may delay or decrease absorption of bendroflumethiazide. Sulfonamide diuretics should be taken at least one hour before or four to six hours after these medications.

Diazoxide-enhanced hyperglycemic, hyperuricemic, and antihypertensive effects. Be cognizant of possible interaction; monitor blood glucose and serum uric acid levels.

Lithium salts-may enhance lithium toxicity due to reduced renal clearance. Avoid concurrent use; if lithium must be prescribed monitor serum lithium levels and adjust lithium dosage accordingly. (See WARNINGS)

MAO inhibitors-dosage adjustments of one or both agents may be necessary since hypotensive effects are enhanced.

Nondepolarizing muscle relaxants, preanesthetics and anesthetics used in surgery (e.g., tubocurarine chloride and gallamine triethiodide)-effects of these agents may be potentiated; dosage adjustments may be required. Monitor and correct any fluid and electrolyte imbalances prior to surgery if feasible.

Nonsteroidal anti-inflammatory agents-in some patients, the administration of a nonsteroidal anti-inflammatory agent can reduce the diuretic, natriuretic, and antihypertensive effect of loop, potassium-sparing or thiazide diuretics. Therefore, when bendroflumethiazide and nonsteroidal anti-inflammatory agents are used concomitantly, the patient should be observed closely to determine if the desired effect of the diuretic is obtained.

Methenamine-possible decreased effectiveness due to alkalinization of the urine.

Pressor amines (e.g., norepinephrine)-decreased arterial responsiveness, but not sufficient to preclude effectiveness of the pressor agent for therapeutic use. Use caution in patients taking both medications who undergo surgery. Administer preanesthetic and anesthetic agents in reduced dosage, and if possible, discontinue bendroflumethiazide one week prior to surgery.

Probenecid or sulfinpyrazone-increased dosage of these agents may be necessary since bendroflumethiazide may have hyperuricemic effects.

Drug/Laboratory Test Interactions

Bendroflumethiazide may produce false-negative results with the phentolamine and tyramine tests; may interfere with the phenosulfonphthalein test due to decreased excretion; and it may cause diagnostic interference of serum electrolyte levels, blood and urine glucose levels, and a decrease in serum PBI levels without signs of thyroid disturbance.

Carcinogenesis, Mutagenesis, Impairment of Fertility

Nadolol

In chronic oral toxicologic studies (one to two years) in mice, rats, and dogs, nadolol did not produce any significant toxic effects. In two-year oral carcinogenicity studies in rats and mice, nadolol did not produce any neoplastic, preneoplastic, or nonneoplastic pathologic lesions. In fertility and general reproductive performance studies in rats, nadolol caused no adverse effect.

Bendroflumethiazide

Studies have not been performed to evaluate carcinogenic potential, mutagenesis, or whether this drug adversely affects fertility in males or females.

PREGNANCY

Pregnancy-Teratogenic Effects

Nadolol

Category C

In animal reproduction studies with nadolol, evidence of embryo- and fetotoxicity was found in rabbits, but not in rats or hamsters, at doses 5 to 10 times greater (on a mg/kg basis) than the maximum indicated human dose. No teratogenic potential was observed in any of these species.

There are no adequate and well-controlled studies in pregnant women. Nadolol should be used during pregnancy only if the potential benefit justifies the potential risk to the fetus. Neonates whose mothers are receiving nadolol at parturition have exhibited bradycardia, hypoglycemia, and associated symptoms.

Bendroflumethiazide

Category C

Animal reproduction studies have not been conducted with bendroflumethiazide. It is also not known whether this drug can cause fetal harm when administered to a pregnant woman or can affect reproduction capacity. Bendroflumethiazide should be given to a pregnant woman only if clearly needed.

Pregnancy-Nonteratogenic Effects

Thiazides cross the placental barrier and appear in cord blood. The use of thiazides in pregnant women requires that the anticipated benefit be weighed against possible hazards to the fetus. These hazards include fetal or neonatal jaundice, thrombocytopenia, and possibly other adverse reactions which have occurred in the adult.

Nursing Mothers

Both nadolol and bendroflumethiazide are excreted in human milk. Because of the potential for serious adverse reactions in nursing infants from both drugs, a decision should be made whether to discontinue nursing or to discontinue therapy taking into account the importance of nadolol and bendroflumethiazide tablets to the mother.

Pediatric Use

Safety and effectiveness in pediatric patients have not been established.

Geriatric Use

Clinical studies of nadolol and bendroflumethiazide tablets did not include sufficient numbers of subjects aged 65 and over to determine whether they respond differently from younger subjects. Other reported clinical experience has not identified differences in responses between the elderly and younger patients. In general, dose selection for an elderly patient should be cautious, usually starting at the low end of the dosing range, reflecting the greater frequency of decreased hepatic, renal, or cardiac function, and of concomitant disease or other drug therapy. This drug is known to be substantially excreted by the kidney, and the risk of toxic reaction to this drug may be greater in patients with impaired function. Because elderly patients are more likely to have decreased renal function, care should be taken in dose selection, and it may be useful to monitor renal function.

ADVERSE REACTIONS

Nadolol

Most adverse effects have been mild and transient and have rarely required withdrawal of therapy.

Cardiovascular-Bradycardia with heart rates of less than 60 beats per minute occurs commonly, and heart rates below 40 beats per minute and/or symptomatic bradycardia were seen in about 2 of 100 patients. Symptoms of peripheral vascular insufficiency, usually of the Raynaud type, have occurred in approximately 2 of 100 patients. Cardiac failure, hypotension, and rhythm/conduction disturbances have each occurred in about 1 of 100 patients. Single instances of first degree and third degree heart block have been reported; intensification of AV block is a known effect of beta-blockers (see also CONTRAINDICATIONS, WARNINGS, and PRECAUTIONS).

Central Nervous System-Dizziness or fatigue has been reported in approximately 2 of 100 patients; paresthesias, sedation, and change in behavior have each been reported in approximately 6 of 1000 patients.

Respiratory-Bronchospasm has been reported in approximately 1 of 1000 patients (see CONTRAINDICATIONS and WARNINGS).

Gastrointestinal-Nausea, diarrhea, abdominal discomfort, constipation, vomiting, indigestion, anorexia, bloating, and flatulence have been reported in 1 to 5 of 1000 patients.

Miscellaneous-Each of the following has been reported in 1 to 5 of 1000 patients: rash; pruritus; headache; dry mouth, eyes, or skin; impotence or decreased libido; facial swelling; weight gain; slurred speech; cough; nasal stuffiness; sweating; tinnitus; blurred vision. Reversible alopecia has been reported infrequently.

The following adverse reactions have been reported in patients taking nadolol and/or other beta-adrenergic blocking agents, but no causal relationship to nadolol has been established.

Central Nervous System-Reversible mental depression progressing to catatonia; visual disturbances; hallucinations; an acute reversible syndrome characterized by disorientation for time and place, short-term memory loss, emotional lability with slightly clouded sensorium, and decreased performance on neuropsychometrics.

Gastrointestinal-Mesenteric arterial thrombosis; ischemic colitis; elevated liver enzymes.

Hematologic-Agranulocytosis; thrombocytopenic or nonthrombocytopenic purpura.

Allergic-Fever combined with aching and sore throat; laryngospasm; respiratory distress.

Miscellaneous-Pemphigoid rash; hypertensive reaction in patients with pheochromocytoma; sleep disturbances; Peyronie's disease.

The oculomucocutaneous syndrome associated with the beta-blocker practolol has not been reported with nadolol.

Bendroflumethiazide

Gastrointestinal-Nausea, vomiting, cramping and anorexia are not uncommon; diarrhea, constipation, gastric irritation, abdominal bloating, jaundice (intrahepatic cholestatic jaundice), hepatitis, and sialadenitis occasionally occur; and pancreatitis has been reported.

Central Nervous System-Dizziness, vertigo, paresthesia, headache, and xanthopsia occasionally occur.

Hematologic-Leukopenia, agranulocytosis, thrombocytopenia, hemolytic anemia, and aplastic anemia have been reported.

Dermatologic-Hypersensitivity-Purpura, exfoliative dermatitis, pruritus, ecchymosis, urticaria, necrotizing angiitis (vasculitis, cutaneous vasculitis), respiratory distress including pneumonitis, fever, and anaphylactic reactions occasionally occur; photosensitivity and rash have been reported.

Cardiovascular-Orthostatic hypotension may occur and may be potentiated by coadministration with certain other drugs (e.g., alcohol, barbiturates, narcotics, other antihypertensive medications, etc.; see PRECAUTIONS, Drug Interactions).

Other-Muscle spasm, weakness, or restlessness is not uncommon; hyperglycemia, glycosuria, metabolic acidosis in diabetic patients, hyperuricemia, allergic glomerulonephritis, and transient blurred vision occasionally occur.

Whenever adverse reactions are moderate or severe, thiazide dosage should be reduced or therapy withdrawn.

To report SUSPECTED ADVERSE REACTIONS, contact IMPAX Laboratories, Inc. at 1-800-934-6729 or FDA at 1-800-FDA-1088 or www.fda.gov/medwatch.

OVERDOSAGE

In the event of overdosage, nadolol may cause excessive bradycardia, cardiac failure, hypotension, or bronchospasm.

In addition to the expected diuresis, overdosage of bendroflumethiazide may produce varying degrees of lethargy which may progress to coma with minimal depression of respiration and cardiovascular function and without significant serum electrolyte changes or dehydration. The mechanism of thiazide-induced CNS depression is unknown. Gastrointestinal irritation may occur. Transitory increase in BUN has been reported, and serum electrolyte changes may occur, especially in patients with impaired renal function.

Treatment

Nadolol can be removed from the general circulation by hemodialysis. In determining the duration of corrective therapy, note must be taken of the long duration of the effect of nadolol. In addition to gastric lavage, the following measures should be employed, as appropriate.

Excessive Bradycardia

Administer atropine (0.25 to 1.0 mg). If there is no response to vagal blockade, administer isoproterenol cautiously.

Cardiac Failure

Administer a digitalis glycoside and diuretic. It has been reported that glucagon may also be useful in this situation.

Hypotension

Administer vasopressors, e.g., epinephrine or levarterenol. (There is evidence that epinephrine may be the drug of choice.)

Bronchospasm

Administer a beta2-stimulating agent and/or a theophylline derivative.

Stupor or Coma

Supportive therapy as warranted.

Gastrointestinal Effects

Symptomatic treatment as needed.

BUN and/or Serum Electrolyte Abnormalities

Institute supportive measures as required to maintain hydration, electrolyte balance, respiration, and cardiovascular and renal function.

DOSAGE AND ADMINISTRATION

DOSAGE MUST BE INDIVIDUALIZED (SEE INDICATIONS). NADOLOL AND BENDROFLUMETHIAZIDE TABLETS MAY BE ADMINISTERED WITHOUT REGARD TO MEALS.

Bendroflumethiazide is usually given at a dose of 5 mg daily. The usual initial dose of nadolol is 40 mg once daily whether used alone or in combination with a diuretic. Bendroflumethiazide in nadolol and bendroflumethiazide tablets is 30 percent more bioavailable than that of 5 mg bendroflumethiazide tablets. Conversion from 5 mg bendroflumethiazide tablets to nadolol and bendroflumethiazide tablets represents a 30 percent increase in dose of bendroflumethiazide.

The initial dose of nadolol and bendroflumethiazide tablets may therefore be the 40 mg/5 mg tablet once daily. When the antihypertensive response is not satisfactory, the dose may be increased by administering the 80 mg/5 mg tablet once daily.

When necessary, another antihypertensive agent may be added gradually beginning with 50 percent of the usual recommended starting dose to avoid an excessive fall in blood pressure.

Dosage Adjustment in Renal Failure

Absorbed nadolol is excreted principally by the kidneys and, although nonrenal elimination does occur, dosage adjustments are necessary in patients with renal impairment. The following dose intervals are recommended:

Creatinine Clearance (mL/min/1.73 m^2) | Dosage Interval (hours)
>50 | 24
31 to 50 | 24 to 36
10 to 30 | 24 to 48
<10 | 40 to 60

HOW SUPPLIED

Nadolol and bendroflumethiazide tablets, 40 mg/5 mg, contain 40 mg nadolol combined with 5 mg bendroflumethiazide, and are white to off-white, round, bi-convex tablets debossed with "G" bisect "531" on one side and plain on the other.

Bottles of 100 | NDC 0115-5311-01
Bottles of 500 | NDC 0115-5311-02

Nadolol and bendroflumethiazide tablets, 80 mg/5 mg, contain 80 mg nadolol combined with 5 mg bendroflumethiazide, and are white to off-white, round, bi-convex tablets debossed with "G" bisect "532" on one side and plain on the other.

Bottles of 100 | NDC 0115-5322-01
Bottles of 500 | NDC 0115-5322-02

Storage

Store at 20°C to 25°C (68°F to 77°F) [see USP Controlled Room Temperature].

Dispense in a tightly-closed, light-resistant container as defined in the USP, with a child-resistant closure, as required.

Dist. by:
Impax Generics
Hayward, CA 94544

522-03
Rev. 11/2015

PRINCIPAL DISPLAY PANEL - 40 mg/5 mg Bottle Label

Impax Generics

NDC 0115-5311-02

Nadolol and
Bendroflumethiazide
Tablets, USP

40 mg/5 mg

Rx only

100 TABLETS

PRINCIPAL DISPLAY PANEL - 80 mg/5 mg Bottle Label

Impax Generics

NDC 0115-5322-02

Nadolol and
Bendroflumethiazide
Tablets, USP

80 mg/5 mg

Rx only

100 TABLETS